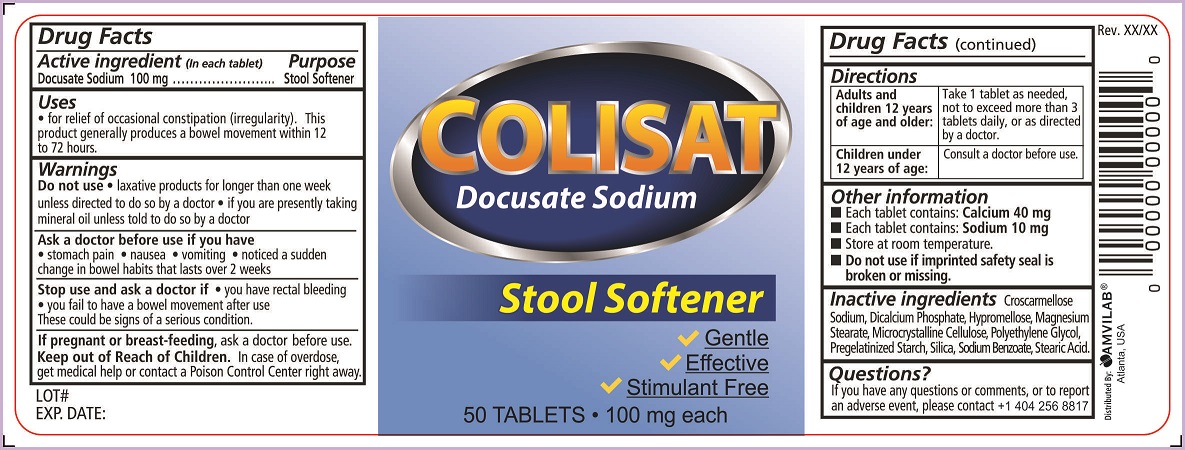 DRUG LABEL: Colistat
NDC: 69975-750 | Form: TABLET, FILM COATED
Manufacturer: Amvilab LLC
Category: otc | Type: HUMAN OTC DRUG LABEL
Date: 20150716

ACTIVE INGREDIENTS: DOCUSATE SODIUM 100 mg/1 1
INACTIVE INGREDIENTS: CROSCARMELLOSE SODIUM; CALCIUM PHOSPHATE, DIBASIC, DIHYDRATE; HYPROMELLOSES; MAGNESIUM STEARATE; CELLULOSE, MICROCRYSTALLINE; POLYETHYLENE GLYCOLS; STARCH, CORN; SILICON DIOXIDE; SODIUM BENZOATE; STEARIC ACID

Drug Facts

Active ingredient (in each tablet)

Docusate Sodium 100 mg

Purpose

Stool Softener

Uses

- for relief of occasional constipation (irregularity).This product generally produces a bowel movement within 12 to 72 hours.

Warnings

Do not use

- laxative products for longer than one week unless directed to do so by a doctor
- if you are presently taking mineral oil unless told to do so by a doctor

Ask a doctor before use if you have

- stomach pain
- nausea
- vomiting
- noticed a sudden change in bowel habits that lasts over 2 weeks

Stop use and ask a doctor if

- you have rectal bleeding
- you fail to have a bowel movement after use

These could be signs of a serious condition.

If pregnant or breast-feeding,

ask a doctor before use.

Keep out of Reach of Children.

In case of overdose, get medical help or contact a Poison Control Center right away.

Directions

Adults and children 12 years of age and older: | Take 1 tablet as needed, not to exceed more than 3 tablets daily, or as directed by a doctor.
Children under 12 years of age: | Consult a doctor before use.

Other information

- Each tablet contains: Calcium 40 mg
- Each tablet contains: Sodium 10 mg
- Store at room temperature.
- Do not use if imprinted safety seal is broken or missing

Inactive ingredients

Croscarmellose Sodium, Dicalcium Phosphate, Hypromellose, Magnesium Stearate, Microcrystalline Cellulose, Polyethylene Glycol, Pregelatinized Starch, Silica, Sodium Benzoate, Stearic Acid.

Questions?

If you have any questions or comments, or to report an adverse event, please contact +1 404 256 8817

Principal Display Panel

COLISTAT

Docusate Sodium

Stool Softener

- Gentle
- Effective
- Stimulant Free

50 TABLETS 100 mg each